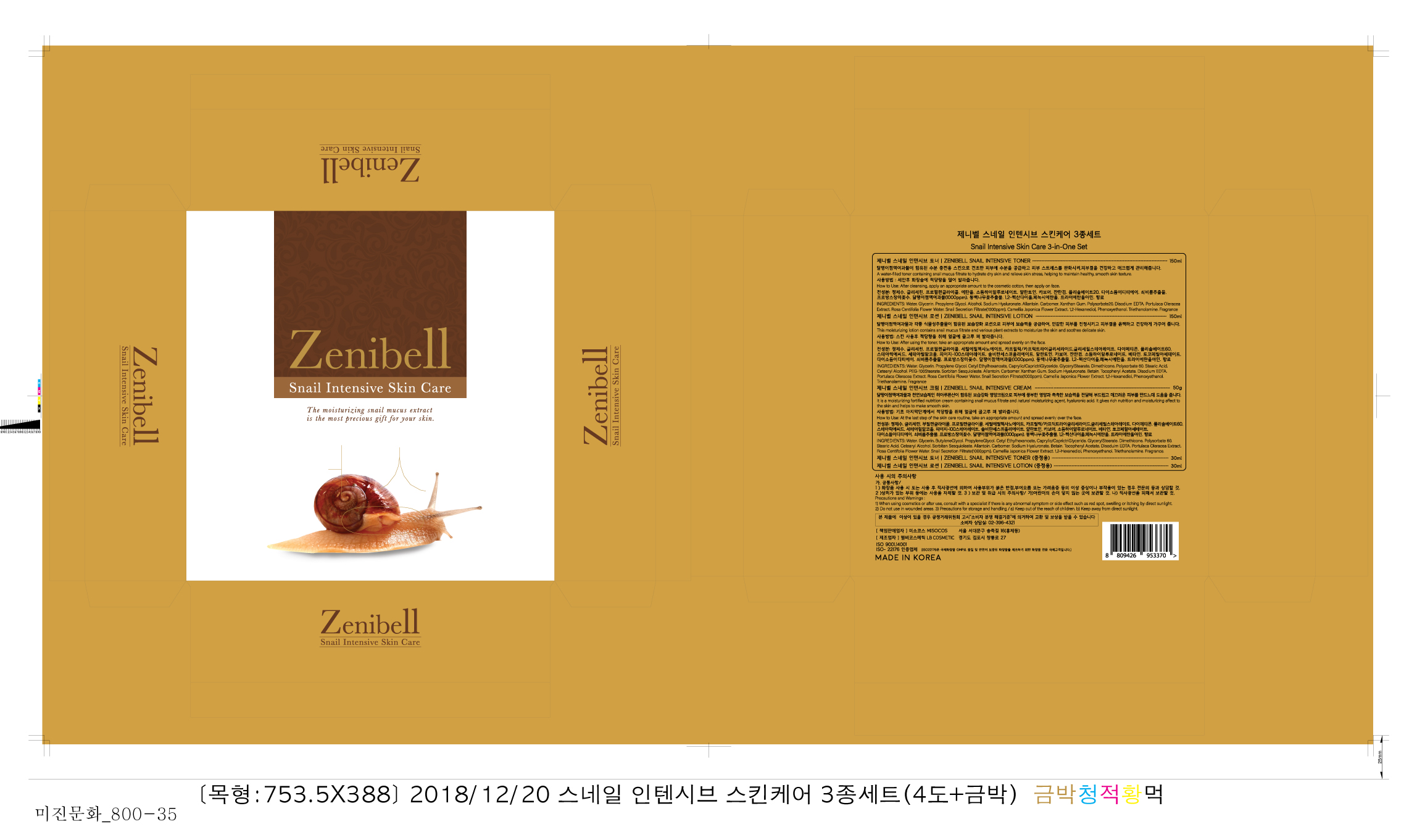 DRUG LABEL: Zenibell Snail Intensive Toner
NDC: 73466-0003 | Form: LIQUID
Manufacturer: MISOCOS
Category: otc | Type: HUMAN OTC DRUG LABEL
Date: 20240705

ACTIVE INGREDIENTS: GLYCERIN 2 g/100 mL
INACTIVE INGREDIENTS: ALLANTOIN; WATER

Drug Facts

ACTIVE INGREDIENT

glycerin

INACTIVE INGREDIENT

propylene glycol, carbomer, allantoin, etc.

PURPOSE

for skin protectant

keep out of reach of the children

INDICATIONS AND USAGE

take a suitable amount on the skin

WARNINGS

■ if following abnormal symptoms occurs after use , stop use and consult with a skin specialist

red specks, swelling, itching

■ don’t use on the part where there is injury, eczema, or dermatitis

Keep out of reach of children

■ if swallowed, get medical help or contact a person control center immediately

DOSAGE AND ADMINISTRATION

for external use only